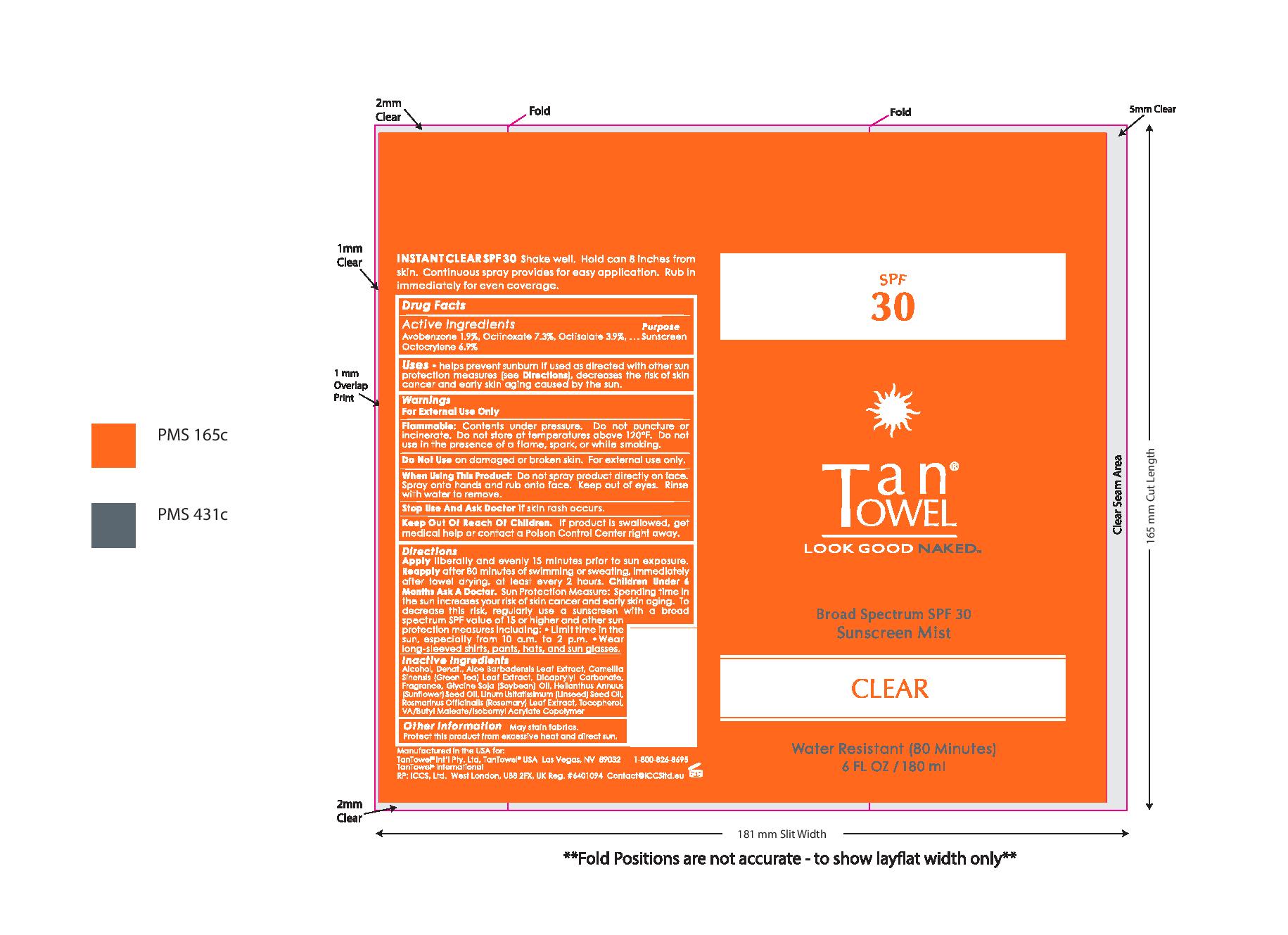 DRUG LABEL: Tan Towel SPF 30 Clear
NDC: 76150-149 | Form: AEROSOL, SPRAY
Manufacturer: Bell International Laboratories
Category: otc | Type: HUMAN OTC DRUG LABEL
Date: 20210114

ACTIVE INGREDIENTS: AVOBENZONE 1.9 g/100 mL; OCTINOXATE 7.3 g/100 mL; OCTISALATE 3.9 g/100 mL; OCTOCRYLENE 6.9 g/100 mL
INACTIVE INGREDIENTS: SOYBEAN OIL; GREEN TEA LEAF; ALCOHOL; DICAPRYLYL CARBONATE; ROSEMARY; TOCOPHEROL; ALOE VERA LEAF; SUNFLOWER OIL; LINSEED OIL

Tan Towel SPF 30 Clear Sunscreen Spray

Active Ingredients.....Purpose

Avobenzone 1.9%, Octinoxate 7.3%, Octisalate 3.9%, Octocrylene 6.9%........Sunscreen

Uses

helps prevent sunburn if used as directed with other sun protection measures (see Directions), decreases the risk of skin cancer and early skin aging caused by the sun.

Warnings

For External Use Only

Flammable: Contents under pressure. Do not puncture or incinerate. Do not store at temperatures above 120oF. Do not use in the presence of a flame, spark, or while smoking.

Do Not Use on damaged or broken skin. For external use only.

When Using This Product: Do not spray product directly on face. Spray onto hands and rub onto face. Keep out of eyes. Rinse with water to remove.

Stop Use And Ask Doctor if skin rash occurs.

Keep Out Of Reach Of Children. If product is swallowed, get medical help or contact a Poison Control Center right away.

Directions

Apply liberally and evenly 15 minutes prior to sun exposure.

Reapply after 80 minutes of swimming or sweating, immediately after towel drying, at least every 2 hours.

Children Under 6 Months Ask A Doctor.

Sun Protection Measure: Spending time in the sun increases your risk of skin cancer and early skin aging. To decrease this risk, regularly use a sunscreen with a broad spectrum value of 15 or higher and other sun protection measures including:

- Limit time in the sun, especially from 10 a.m. to 2 p.m.
- Wear long-sleeved shirts, pants, hats, and sun glasses.

Inactive Ingredients

Alcohol, Denat., Aloe Barbadensis Leaf Extract, Camellia Sinensis (Green Tea) Leaf Extract, Dicaprylyl Carbonate, Fragrance, Glycine Soja (Soybean) Oil, Helianthus Annuus (Sunflower) Seed Oil, Linum Usitatissimum (Linseed) Seed Oil, Rosmarinus Officinalis (Rosemary) Leaf Extract, Tocopherol, VA/Butyl Maleate/Isobornyl Acrylate Copolymer

Other Information

May stain fabrics. Protect this product from excessive heat and direct sun.